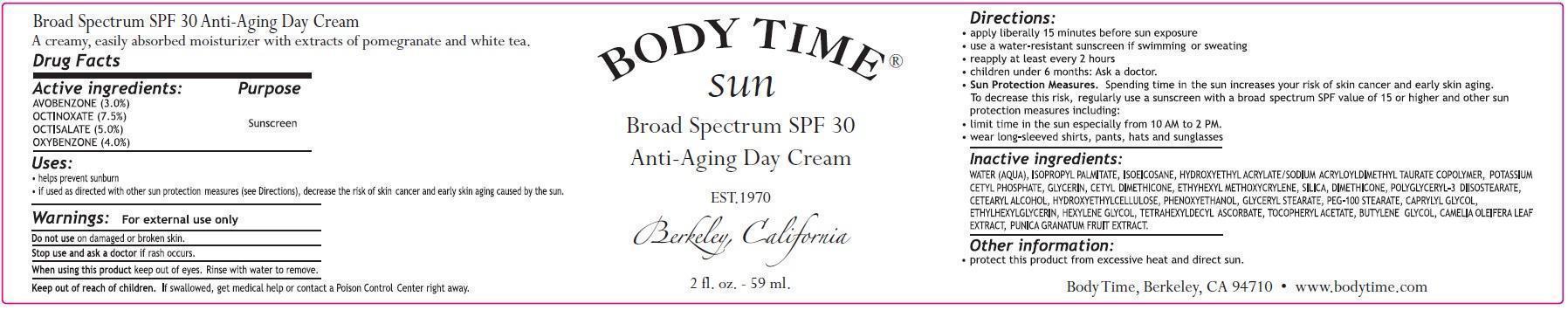 DRUG LABEL: Body Time Sun Broad Spectrum SPF30 Anti-Aging Day
NDC: 61979-002 | Form: CREAM
Manufacturer: Bela Vida Holdings, LLC dba Body Time
Category: otc | Type: HUMAN OTC DRUG LABEL
Date: 20171228

ACTIVE INGREDIENTS: AVOBENZONE 30 mg/1 mL; OCTINOXATE 75 mg/1 mL; OCTISALATE 50 mg/1 mL; OXYBENZONE 40 mg/1 mL
INACTIVE INGREDIENTS: WATER; ISOPROPYL PALMITATE; ISOEICOSANE; POTASSIUM CETYL PHOSPHATE; GLYCERIN; ETHYLHEXYL METHOXYCRYLENE; SILICON DIOXIDE; DIMETHICONE; POLYGLYCERYL-3 DIISOSTEARATE; CETOSTEARYL ALCOHOL; HYDROXYMETHYL CELLULOSE; PHENOXYETHANOL; GLYCERYL MONOSTEARATE; PEG-100 STEARATE; CAPRYLYL GLYCOL; ETHYLHEXYLGLYCERIN; HEXYLENE GLYCOL; TETRAHEXYLDECYL ASCORBATE; .ALPHA.-TOCOPHEROL ACETATE; BUTYLENE GLYCOL; CAMELLIA OLEIFERA LEAF; POMEGRANATE

Body Time Sun Broad Spectrum SPF30 Anti-Aging Day

Active ingredients:

Avobenzone (3.0%)

Octinoxate (7.5%)

Octisalate (5.0%)

Oxybenzone (4.0%)

Purpose

Sunscreen

Uses:

- helps prevent sunburn
- if used as directed with other sun protection measures (see Directions), decrease the risk of skin cancer and early skin aging caused by the sun.

Warnings:

For external use only

Do not use

on damaged or broken skin.

Stop use and ask a doctor

if rash occurs.

When using this product

keep out of eyes. Rinse with water to remove.

Keep out of reach of children.

If swallowed, get medical help or contact a Poison Control Center right away.

Directions:

- apply liberally 15 minutes before sun exposure
- use a water-resistant sunscreen if swimming or sweating
- reapply at least every 2 hours
- children under 6 months: Ask a doctor.
- Sun Protection Measures.Spending time in the sun increases your risk of skin cancer and early skin aging. To decrease this risk, regularly use a sunscreen with a broad spectrum SPF value of 15 or higher and other sun protection measures including:
- limit time in the sun especially from 10 AM to 2 PM.
- wear long-sleeved shirts, pants, hats and sunglasses

Inactive ingredients:

WATER (AQUA), ISOPROPYL PALMITATE, ISOEICOSANE, HYDROXYETHYL ACRYLATE/SODIUM ACRYLOYLDIMETHYL TAURATE COPOLYMER, POTASSIUM CETYL PHOSPHATE, GLYCERIN, CETYL DIMETHICONE, ETHYHEXYL METHOXYCRYLENE, SILICA, DIMETHICONE, POLYGLYCERYL-3 DIISOSTEARATE, CETEARYL ALCOHOL, HYDROXYETHYLCELLULOSE, PHENOXYETHANOL, GLYCERYL STEARATE, PEG-100 STEARATE, CAPRYLYL GLYCOL, ETHYLHEXYLGLYCERIN, HEXYLENE GLYCOL, TETRAHEXYLDECYL ASCORBATE, TOCOPHERYL ACETATE, BUTYLENE GLYCOL, CAMELIA OLEIFERA LEAF EXTRACT, PUNICA GRANATUM FRUIT EXTRACT.

Other information:

- protect this product from excessive heat and direct sun.